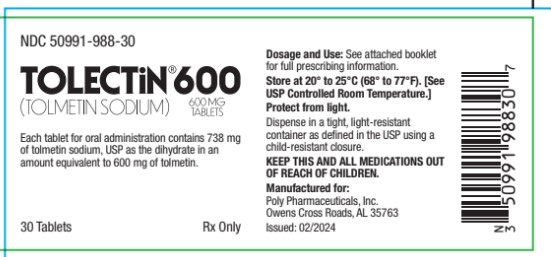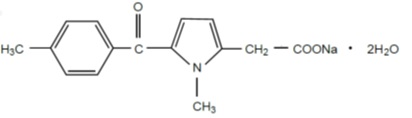 DRUG LABEL: Tolectin
NDC: 50991-988 | Form: TABLET, FILM COATED
Manufacturer: Poly Pharmaceuticals, Inc.
Category: prescription | Type: HUMAN PRESCRIPTION DRUG LABEL
Date: 20251230

ACTIVE INGREDIENTS: TOLMETIN SODIUM 600 mg/1 1
INACTIVE INGREDIENTS: MAGNESIUM STEARATE; SODIUM LAURYL SULFATE; POVIDONE; FERROSOFERRIC OXIDE; FERRIC OXIDE YELLOW; POLYDEXTROSE; TITANIUM DIOXIDE; TRIACETIN; CROSPOVIDONE; MICROCRYSTALLINE CELLULOSE; STARCH, CORN; HYPROMELLOSE, UNSPECIFIED; POLYETHYLENE GLYCOL, UNSPECIFIED

Tolmetin Sodium Tablets, USP 600 mg
Rx only

BOXED WARNING

Cardiovascular Thrombotic Events
• Nonsteroidal anti-inflammatory drugs (NSAIDs) cause an increased risk of serious cardiovascular thrombotic events, including myocardial infarction and stroke, which can be fatal. This risk may occur early in treatment and may increase with duration of use (see WARNINGSand PRECAUTIONS).
• TOLECTIN tablets are contraindicated in the setting of coronary artery bypass graft (CABG) surgery (see CONTRAINDICATIONSand WARNINGS).
Gastrointestinal Risk
• NSAIDs cause an increased risk of serious gastrointestinal adverse events including bleeding, ulceration, and perforation of the stomach or intestines, which can be fatal. These events can occur at any time during use and without warning symptoms. Elderly patients are at greater risk for serious gastrointestinal events (see WARNINGS).

DESCRIPTION

Each tablet for oral administration contains 738 mg of tolmetin sodium, USP as the dihydrate in an amount equivalent to 600 mg of tolmetin. Each tablet contains 54 mg (2.35 mEq) of sodium and the following inactive ingredients: black iron oxide, crospovidone, hypromellose, magnesium stearate, microcrystalline cellulose, polydextrose, polyethylene glycol, povidone, pregelatinized starch (maize), sodium lauryl sulfate, titanium dioxide, triacetin and yellow iron oxide.

The pKa of tolmetin is 3.5 and tolmetin sodium is freely soluble in water, soluble in methanol and slightly soluble in alcohol. Tolmetin sodium is a nonselective nonsteroidal anti-inflammatory agent. The structural formula is:

(C15H14NNaO3• 2H2O)
M.W. 315.30
Sodium 1-methyl-5 p-toluoylpyrrole-2-acetate dihydrate.

CLINICAL PHARMACOLOGY

Studies in animals have shown TOLECTIN (tolmetin sodium) to possess anti-inflammatory, analgesic, and antipyretic activity. In the rat, TOLECTIN prevents the development of experimentally induced polyarthritis and also decreases established inflammation.

The mode of action of TOLECTIN is not known. However, studies in laboratory animals and man have demonstrated that the anti-inflammatory action of TOLECTIN is not due to pituitary- adrenal stimulation. TOLECTIN inhibits prostaglandin synthetase in vitro and lowers the plasma level of prostaglandin E in man. This reduction in prostaglandin synthesis may be responsible for the anti-inflammatory action. TOLECTIN does not appear to alter the course of the underlying disease in man.

In patients with rheumatoid arthritis and in normal volunteers, TOLECTIN is rapidly and almost completely absorbed with peak plasma levels being reached within 30 to 60 minutes after an oral therapeutic dose. In controlled studies, the time to reach peak tolmetin plasma concentration is approximately 20 minutes longer following administration of a 600 mg tablet, compared to an equivalent dose given as 200 mg tablets. The clinical meaningfulness of this finding, if any, is unknown. Tolmetin displays a biphasic elimination from the plasma consisting of a rapid phase with a half-life of 1 to 2 hours followed by a slower phase with a half-life of about 5 hours. Peak plasma levels of approximately 40 mcg/mL are obtained with a 400 mg oral dose. Essentially all of the administered dose isrecovered in the urine in 24 hours either as an inactive oxidative metabolite or as conjugates of tolmetin. An 18-day multiple- dose study demonstrated no accumulation of tolmetin when compared with a single dose.

In two fecal blood loss studies of 4 to 6 days duration involving 15 subjects each, TOLECTIN did not induce an increase in blood loss over that observed during a 4-day drug free control period. In the same studies, aspirin produced a greater blood loss than occurred during the drug free control period, and a greater blood loss than occurred during the TOLECTIN treatment period. In one of the two studies, indomethacin produced a greater fecal blood loss than occurred during the drug free control period; in the second study, indomethacin did not induce a significant increase in blood loss.

TOLECTIN is effective in treating both the acute flares and in the long-term management of the symptoms of rheumatoid arthritis, osteoarthritis and juvenile rheumatoid arthritis.

In patients with either rheumatoid arthritis or osteoarthritis, TOLECTIN is as effective as aspirin and indomethacin in controlling disease activity, but the frequency of the milder gastrointestinal adverse effects and tinnitus was less than in aspirin-treated patients, and the incidence of central nervous system adverse effects was less than in indomethacin-treated patients.

In patients with juvenile rheumatoid arthritis, TOLECTIN is as effective as aspirin in controlling disease activity, with a similar incidence of adverse reactions. Mean SGOT values, initially elevated in patients on previous aspirin therapy, remained elevated in the aspirin group and decreased in the TOLECTIN group.

TOLECTIN has produced additional therapeutic benefit when added to a regimen of gold salts and, to a lesser extent, with corticosteroids. TOLECTIN should not be used in conjunction with salicylates since greater benefit from the combination is not likely, but the potential for adverse reactions is increased.

INDICATIONS & USAGE

Carefully consider the potential benefits and risks of TOLECTIN tablets, USP and other treatment options before deciding to use TOLECTIN tablets. Use the lowest effective dose for the shortest duration consistent with individual patient treatment goals (see WARNINGS).

TOLECTIN tablets are indicated for the relief of signs and symptoms of rheumatoid arthritis and osteoarthritis. TOLECTIN tablets are indicated in the treatment of acute flares and the long-term management of the chronic disease.

TOLECTIN tablets are also indicated for treatment of juvenile rheumatoid arthritis. The safety and effectiveness of TOLECTIN tablets have not been established in pediatric patients under 2 years of age (see PRECAUTIONS: Pediatric Useand DOSAGE AND ADMINISTRATION).

CONTRAINDICATIONS

TOLECTIN tablets are contraindicated in patients with known hypersensitivity to tolmetin sodium.
TOLECTIN should not be given to patients who have experienced asthma, urticaria or allergic-type reactions after taking aspirin or other NSAIDs. Severe, rarely fatal, anaphylactic-like reactions to NSAIDs have been reported in such
patients (see WARNINGS: Anaphylactoid Reactionsand PRECAUTIONS: General: Preexisting Asthma).
TOLECTIN is contraindicated in the setting of coronary artery bypass graft (CABG) surgery (see WARNINGS).

WARNINGS

Cardiovascular Effects

Cardiovascular Thrombotic Events
Clinical trials of several COX-2 selective and nonselective NSAIDs of up to 3 years duration have shown an increased risk of serious cardiovascular (CV) thrombotic events, including myocardial infarction (MI) and stroke, which can be fatal. Based on available data, it is unclear that the risk for CV thrombotic events is similar for all NSAIDs. The relative increase in serious CV thrombotic events over baseline conferred by NSAID use appears to be similar in those with
and without known CV disease or risk factors for CV disease. However, patients with known CV disease or risk factors had a higher absolute incidence of excess serious CV thrombotic events, due to their increased baseline rate. Some observational studies found that this increased risk of serious CV thrombotic events began as early as the first weeks of treatment. The increase in CV thrombotic risk has been observed most consistently at higher doses.
To minimize the potential risk for an adverse CV event in NSAID-treated patients, use the lowest effective dose for the shortest duration possible. Physicians and patients should remain alert for the development of such events, throughout the entire treatment course, even in the absence of previous CV symptoms. Patients should be informed about the symptoms of serious CV events and the steps to take if they occur.
There is no consistent evidence that concurrent use of aspirin mitigates the increased risk of serious CV thrombotic events associated with NSAID use. The concurrent use of aspirin and an NSAID, such as tolmetin, increases the risk of
serious gastrointestinal (GI) events (see WARNINGS).
Status Post Coronary Artery Bypass Graft (CABG) Surgery:Two large, controlled clinical trials of a COX-2 selective NSAID for the treatment of pain in the first 10 to 14 days following CABG surgery found an increased incidence of myocardial infarction and stroke. NSAIDs are contraindicated in the setting of CABG (see CONTRAINDICATIONS).
Post-MI Patients:Observational studies conducted in the Danish National Registry have demonstrated that patients treated with NSAIDs in the post-MI period were at increased risk of reinfarction, CV-related death, and all-cause mortality beginning in the first week of treatment. In this same cohort, the incidence of death in the first year post MI was 20 per 100 person years in NSAID-treated patients compared to 12 per 100 person years in non-NSAID exposed patients. Although the absolute rate of death declined somewhat after the first year post-MI, the increased relative risk of death in NSAID users persisted over at least the next 4 years of follow-up.
Avoid the use of TOLECTIN in patients with a recent MI unless the benefits are expected to outweigh the risk of recurrent CV thrombotic events. If TOLECTIN is used in patients with a recent MI, monitor patients for signs of cardiac ischemia.
Hypertension:NSAIDs, including TOLECTIN, can lead to onset of new hypertension or worsening of preexisting hypertension, either of which may contribute to the increased incidence of CV events. Patients taking thiazides or loop diuretics may have impaired response to these therapies when taking NSAIDs. NSAIDs, including TOLECTIN, should be used with caution in patients with hypertension. Blood pressure (BP) should be monitored closely during the initiation of NSAID treatment and throughout the course of therapy.
Heart Failure and Edema:The Coxib and traditional NSAID Trialists’ Collaboration meta-analysis of randomized controlled trials demonstrated an approximately two-fold increase in hospitalizations for heart failure in COX-2 selective-treated patients and nonselective NSAID-treated patients compared to placebo-treated patients. In a Danish National Registry study of patients with heart failure, NSAID use increased the risk of MI, hospitalization for heart failure, and death.
Additionally, fluid retention and edema have been observed in some patients treated with NSAIDs. Use of tolmetin may blunt the CV effects of several therapeutic agents used to treat these medical conditions [e.g., diuretics, ACE
inhibitors, or angiotensin receptor blockers (ARBs)] (see PRECAUTIONS: Drug Interactions).
Avoid the use of TOLECTIN in patients with severe heart failure unless the benefits are expected to outweigh the risk of worsening heart failure. If TOLECTIN is used in patients with severe heart failure, monitor patients for signs of worsening heart failure.

Gastrointestinal (GI) Effects

Risk of Ulceration, Bleeding, and Perforation:NSAIDs, including TOLECTIN, can cause serious gastrointestinal adverse events including inflammation, bleeding, ulceration, and perforation of the stomach, small intestine or large intestine, which can be fatal. These serious adverse events can occur at any time, with or without warning symptoms in patients treated with NSAIDs. Only one in five patients who develop a serious upper GI adverse event on NSAID therapy is symptomatic. Upper GI ulcers, gross bleeding, or perforation caused by NSAIDs occur in approximately 1% of patients treated for 3 to 6 months, and in about 2% to 4% of patients treated for one year. These trends continue with longer duration of use, increasing the likelihood of developing a serious GI event at some time during the course of therapy. However, even short-term therapy is not without risk.
NSAIDs should be prescribed with extreme caution in those with a prior history of ulcer disease or gastrointestinal bleeding. Patients with a prior history of peptic ulcer disease and/or gastrointestinal bleedingwho use NSAIDs have a greater than 10-fold increased risk for developing a GI bleed compared to patients with neither of these risk factors. Other factors that increase the risk for GI bleeding in patients treated with NSAIDs include concomitant use of oral corticosteroids or anticoagulants, longer duration of NSAID therapy, smoking, use of alcohol, older age, and poor general health status. Most spontaneous reports of fatal GI events are in elderly or debilitated patients and therefore, special care should be taken in treating this population.
To minimize the potential risk for an adverse GI event in patients treated with an NSAID, the lowest effective dose should be used for the shortest possible duration. Patients and physicians should remain alert for signs and symptoms of GI ulceration and bleeding during NSAID therapy and promptly initiate additional evaluation and treatment if a serious GI adverse event is suspected. This should include discontinuation of the NSAID until a serious GI adverse event is ruled out. For high risk patients, alternate therapies that do not involve NSAIDs should be considered.

Renal Effects

Long-term administration of NSAIDs has resulted in renal papillary necrosis and other renal injury. Acute interstitial nephritis with hematuria, proteinuria, and occasionally nephrotic syndrome have been reported in patients treated with TOLECTIN.
Renal toxicity has also been seen in patients in whom renal prostaglandins have a compensatory role in the maintenance of renal perfusion. In these patients, administration of an NSAID may cause a dose dependent reduction in prostaglandin formation and, secondarily, in renal blood flow, which may precipitate overt renal decompensation. Patients at greatest risk of this reaction are those with impaired renal function, heart failure, liver dysfunction, those taking diuretics and ACE inhibitors and the elderly. Discontinuation of NSAID therapy is usually followed by recovery to the pretreatment state.
Advanced Renal Disease:No information is available from controlled clinical trials regarding the use of TOLECTIN in patients with advanced renal disease. Therefore, treatment with TOLECTIN is not recommended in these patients with
advanced renal disease. If TOLECTIN therapy must be initiated, close monitoring of the patient’s renal function is advisable.

Anaphylactoid Reactions

As with other NSAIDs, anaphylactoid reactions may occur in patients with known prior exposure to TOLECTIN. TOLECTIN should not be given to patients with the aspirin triad. This symptom complex typically occurs in asthmatic patients who experience rhinitis with or without nasal polyps, or who exhibit severe, potentially fatal bronchospasm after taking aspirin or other NSAIDs (see CONTRAINDICATIONSand PRECAUTIONS: General: Preexisting Asthma). Emergency help should be sought in cases where an anaphylactoid reaction occurs.

Skin Reactions

NSAIDs, including TOLECTIN, can cause serious skin adverse events such as exfoliative dermatitis, Stevens-Johnson Syndrome (SJS), and toxic epidermal necrolysis (TEN), which can be fatal. These serious events may occur without warning. Patients should be informed about the signs and symptoms of serious skin manifestations and use of the drug should be discontinued at the first appearance of skin rash or any other sign of hypersensitivity.

Drug Reaction with Eosinophilia and Systemic Symptoms (DRESS) has been reported in patients taking NSAIDs such as TOLECTIN sodium tablets. Some of these events have been fatal or life-threatening. DRESS typically, although not
exclusively, presents with fever, rash, lymphadenopathy, and/or facial swelling. Other clinical manifestations may include hepatitis, nephritis, hematological abnormalities, myocarditis, or myositis. Sometimes symptoms of DRESS may resemble an acute viral infection. Eosinophilia is often present. Because this disorder is variable in its presentation, other organ systems not noted here may be involved. It is important to note that early manifestations of hypersensitivity, such as fever or lymphadenopathy, may be present even though rash is not evident. If such signs or symptoms are present, discontinue TOLECTIN and evaluate the patient immediately.

Fetal Toxicity

Premature Closure of Fetal Ductus Arteriosus:Avoid use of NSAIDs, including TOLECTIN, in pregnant women at about 30 weeks gestation and later. NSAIDs including TOLECTIN, increase the risk of premature closure of the fetal ductus arteriosus at approximately this gestational age.
Oligohydramnios/Neonatal Renal Impairment:Use of NSAIDs, including tolmetin sodium tablets, at about 20 weeks gestation or later in pregnancy may cause fetal renal dysfunction leading to oligohydramnios and, in some cases,
neonatal renal impairment. These adverse outcomes are seen, on average, after days to weeks of treatment, although oligohydramnios has been infrequently reported as soon as 48 hours after NSAID initiation. Oligohydramnios is often,
but not always, reversible with treatment discontinuation. Complications of prolonged oligohydramnios may, for example, include limb contractures and delayed lung maturation. In some postmarketing cases of impaired neonatal renal function, invasive procedures such as exchange transfusion or dialysis were required.
If NSAID treatment is necessary between about 20 weeks and 30 weeks gestation, limit TOLECTIN use to the lowest effective dose and shortest duration possible. Consider ultrasound monitoring of amniotic fluid if TOLECTIN treatment extends beyond 48 hours. Discontinue TOLECTIN if oligohydramnios occurs and follow up according to clinical practice (see PRECAUTIONS: Pregnancy).

PRECAUTIONS

GENERAL PRECAUTIONS

TOLECTIN cannot be expected to substitute for corticosteroids or to treat corticosteroid insufficiency. Abrupt discontinuation of corticosteroids may lead to disease exacerbation. Patients on prolonged corticosteroid therapy should have their therapy tapered slowly if a decision is made to discontinue corticosteroids.
The pharmacological activity of TOLECTIN in reducing fever and inflammation may diminish the utility of these diagnostic signs in detecting complications of presumed noninfectious, painful conditions.
Opthalmological Effects:Because of ocular changes observed in animals and of reports of adverse eye findings with NSAIDs, it is recommended that patients who develop visual disturbances during treatment with TOLECTIN have
ophthalmologic evaluations.
Hepatic Effects:Borderline elevations of one or more liver tests may occur in up to 15% of patients taking NSAIDs including TOLECTIN. These laboratory abnormalities may progress, may remain unchanged, or may be transient with
continuing therapy. Notable elevations of ALT or AST (approximately three or more times the upper limit of normal) have been reported in approximately 1% of patients in clinical trials with NSAIDs. In addition, rare cases of severe hepatic
reactions, including jaundice and fatal fulminant hepatitis, liver necrosis, and hepatic failure, some of them with fatal outcomes have been reported.
A patient with symptoms and/or signs suggesting liver dysfunction, or in whom an abnormal liver test has occurred should be evaluated for evidence of the development of a more severe hepatic reaction while on therapy with TOLECTIN.
If clinical signs and symptoms consistent with liver disease develop, or if systemic manifestations occur (e.g., eosinophilia, rash, etc.), TOLECTIN should be discontinued.
Hematological Effects:Anemia is sometimes seen in patients receiving NSAIDs including TOLECTIN. This may be due to fluid retention, occult or gross GI blood loss, or an incompletely described effect upon erythropoiesis. Patients
on long-term treatment with NSAIDs, including tolmetin, should have their hemoglobin or hematocrit checked if they exhibit any signs or symptoms of anemia. NSAIDs inhibit platelet aggregation and have been shown to prolong
bleeding time in some patients. Unlike aspirin, their effect on platelet function is quantitatively less, of shorter duration, and reversible. Patients receiving TOLECTIN who may be adversely affected by alterations in platelet function, such as those with coagulation disorders or patients receiving anticoagulants, should be carefully monitored.
Preexisting Asthma:Patients with asthma may have aspirin-sensitive asthma. The use of aspirin in patients with aspirin-sensitive asthma has been associated with severe bronchospasm which can be fatal. Since cross-reactivity, including bronchospasm, between aspirin and other NSAIDs has been reported in such aspirin-sensitive patients, tolmetin should not be administered to patients with this form of aspirin sensitivity and should be used with caution in patients with preexisting asthma.

INFORMATION FOR PATIENTS

Patients should be informed of the following information before initiating therapy with an NSAID and periodically during the course of ongoing therapy. Patients should also be encouraged to read the NSAID Medication Guide that accompanies each prescription dispensed.
1. Cardiovascular Thrombotic Events:Advise patients to be alert for the symptoms of cardiovascular thrombotic events, including chest pain, shortness of breath, weakness, or slurring of speech, and to report any of these symptoms to their healthcare provider immediately (see WARNINGS).
2. TOLECTIN, like other NSAIDs, can cause GI discomfort and, rarely, serious GI side effects, such as ulcers and bleeding, which may result in hospitalization and even death. Although serious GI tract ulcerations and bleeding can occur without warning symptoms, patients should be alert for the signs and symptoms of ulcerations and bleeding, and should ask for medical advice when observing any indicative signs or symptoms including epigastric pain, dyspepsia, melena, and hematemesis. Patients should be apprised of the importance of this follow-up (see WARNINGS: Gastrointestinal (GI) Effects: Risk of Ulceration, Bleeding, and Perforation).
3. Serious Skin Reactions, including DRESS:Advise patients to stop taking TOLECTIN sodium tablets immediately if they develop any type of rash or fever and to contact their healthcare provider as soon as possible (see WARNINGS).
4. Heart Failure And Edema:Advise patients to be alert for the symptoms of congestive heart failure including shortness of breath, unexplained weight gain, or edema and to contact their healthcare provider if such symptoms occur (see WARNINGS).
5. Patients should be informed of the warning signs and symptoms of hepatotoxicity (e.g., nausea, fatigue, lethargy, pruritus, jaundice, right upper quadrant tenderness, and “flu-like” symptoms). If these occur, patients should be instructed to stop therapy and seek immediate medical therapy.
6. Patients should be informed of the signs of an anaphylactoid reaction (e.g., difficulty breathing, swelling of the face or throat). If these occur, patients should be instructed to seek immediate emergency help (see WARNINGS).
7. Fetal Toxicity:Inform pregnant women to avoid use of TOLECTIN sodium tablets and other NSAIDs starting at 30 weeks gestation because of the risk of the premature closing of the fetal ductus arteriosus. If treatment with tolmetin sodium tablets is needed for a pregnant woman between about 20 to 30 weeks gestation, advise her that she may need to be monitored for oligohydramnios, if treatment continues for longer than 48 hours (see WARNINGS: Fetal Toxicity, PRECAUTIONS: Pregnancy).

LABORATORY TESTS

Because serious GI tract ulcerations and bleeding can occur without warning symptoms, physicians should monitor for signs or symptoms of GI bleeding. Patients on long-term treatment with NSAIDs should have their CBC and a chemistry profile checked periodically. If clinical signs and symptoms consistent with liver or renal disease develop, systemic manifestations occur (e.g., eosinophilia, rash, etc.) or if abnormal liver tests persist or worsen, tolmetin should be discontinued.

DRUG INTERACTIONS

ACE Inhibitors:Reports suggest that NSAIDs may diminish the antihypertensive effect of ACE Inhibitors. This interaction should be given consideration in patients taking NSAIDs concomitantly with ACE Inhibitors.
Aspirin:As with other NSAIDs, concomitant administration of TOLECTIN sodium and aspirin is not generally recommended because of the potential of increased adverse effects.
Diuretics:Clinical studies, as well as post-marketing observations have shown that NSAIDs can reduce the natriuretic effect of furosemide and thiazides in some patients. This response has been attributed to inhibition of renal prostaglandin synthesis. During concomitant therapy with NSAIDs, the patient should be observed closely for signs of renal failure, as well as to assure diuretic efficacy.
Lithium:NSAIDs have produced an elevation of plasma lithium levels and a reduction in renal lithium clearance. The mean minimum lithium concentration increased 15% and the renal clearance was decreased by approximately 20%. These effects have been attributed to inhibition of renal prostaglandin synthesis by the NSAID. Thus, when NSAIDs and lithium are administered concurrently, subjects should be observed carefully for signs of lithium toxicity.
Methotrexate:NSAIDs have been reported to competitively inhibit methotrexate accumulation in rabbit kidney slices. This may indicate that they could enhance the toxicity of methotrexate. Caution should be used when NSAIDs are
administered concomitantly with methotrexate.
Warfarin:The effects of warfarin and NSAIDs on GI bleeding are synergistic, such that users of both drugs together have a risk of serious GI bleeding higher than users of either drug alone.
The in vitrobinding of warfarin to human plasma proteins is unaffected by TOLECTIN, and TOLECTIN does not alter the prothrombin time of normal volunteers. However, increased prothrombin time and bleeding have been reported in patients on concomitant tolmetin and warfarin therapy. Therefore, caution should be exercised when administering tolmetin to patients on anticoagulants.
Hypoglycemic Agents:In adult diabetic patients under treatment with either sulfonylureas or insulin there is no change in the clinical effects of either TOLECTIN or the hypoglycemic agents.

DRUG & OR LABORATORY TEST INTERACTIONS

The metabolites of TOLECTIN in urine have been found to give positive tests for proteinuria using tests which rely on acid precipitation as their endpoint (e.g., sulfosalicylic acid). No interference is seen in the tests for proteinuria using dye-impregnated commercially available reagent strips (e.g., Albustix®, Uristix®, etc.).

Drug-Food Interactions

In a controlled single-dose study, administration of TOLECTIN with milk had no effect on peak plasma tolmetin concentrations, but decreased total tolmetin bioavailability by 16%. When TOLECTIN was taken immediately after a meal, peak plasma tolmetin concentrations were reduced by 50% while total bioavailability was again decreased by 16%.

CARCINOGENESIS & MUTAGENESIS & IMPAIRMENT OF FERTILITY

Tolmetin sodium did not possess any carcinogenic liability in the following long-term studies: a 24-month study in rats at doses as high as 75 mg/kg/day, and an 18-month study in mice at doses as high as 50 mg/kg/day.
No mutagenic potential of TOLECTIN was found in the Ames Salmonella-Microsomal Activation Test.
Reproductive studies revealed no impairment of fertility in animals. Effects on parturition have been shown, however, as with other prostaglandin inhibitors. This information is detailed in the Pregnancy section.

PREGNANCY

Risk Summary:Use of NSAIDs, including TOLECTIN, can cause premature closure of the fetal ductus arteriosus and fetal renal dysfunction leading to oligohydramnios and, in some cases, neonatal renal impairment. Because of these risks, limit dose and duration of TOLECTIN use between about 20 and 30 weeks of gestation, and avoid TOLECTIN use at about 30 weeks of gestation and later in pregnancy (see WARNINGS: Fetal Toxicity).
Premature Closure of Fetal Ductus Arteriosus:Use of NSAIDs, including TOLECTIN, at about 30 weeks gestation or later in pregnancy increases the risk of premature closure of the fetal ductus arteriosus.
Oligohydramnios/Neonatal Renal Impairment:Use of NSAIDs at about 20 weeks gestation or later in pregnancy has been associated with cases of fetal renal dysfunction leading to oligohydramnios, and in some cases, neonatal renal
impairment.
Data from observational studies regarding other potential embryofetal risks of NSAID use in women in the first or second trimesters of pregnancy are inconclusive. In animal reproduction studies in rats and rabbits at doses up to 50 mg/kg (1.5 times the maximum clinical dose based on a body weight of 60 kg) there revealed no evidence of teratogenesis or impaired fertility due to tolmetin. However, animal reproduction studies are not always predictive of human response. Based on animal data, prostaglandins have been shown to have an important role in endometrial vascular permeability, blastocyst implantation, and decidualization. In animal studies, administration of prostaglandin synthesis inhibitors such as tolmetin, resulted in increased pre- and post-implantation loss. Prostaglandins also have been shown to have an important role in fetal kidney development. In published animal studies, prostaglandin synthesis inhibitors have been reported to impair kidney development when administered at clinically relevant doses. The estimated background risk of major birth defects and miscarriage for the indicated population(s) is unknown. All pregnancies have a background risk of birth defect, loss, or other adverse outcomes. In the U.S. general population, the estimated background risk of major birth defects and miscarriage in clinically recognized pregnancies is 2 to 4% and 15 to 20%, respectively.
Clinical Considerations: Fetal/Neonatal Adverse Reactions: Premature Closure of Fetal Ductus Arteriosus:Avoid use of NSAIDs in women at about 30 weeks gestation and later in pregnancy, because NSAIDs, including TOLECTIN, can cause premature closure of the fetal ductus arteriosus (see WARNINGS: Fetal Toxicity).
Oligohydramnios/Neonatal Renal Impairment:If an NSAID is necessary at about 20 weeks gestation or later in pregnancy, limit the use to the lowest effective dose and shortest duration possible. If TOLECTIN treatment extends beyond 48 hours, consider monitoring with ultrasound for oligohydramnios. If oligohydramnios occurs, discontinue tolmetin sodium tablets and follow up according to clinical practice (see WARNINGS: Fetal Toxicity).
Data: Human Data:There are no adequate, well controlled studies in pregnant women. TOLECTIN should be used in pregnancy only if the potential benefit justifies the potential risk to the fetus.
Premature Closure of Fetal Ductus Arteriosus:Published literature reports that the use of NSAIDs at about 30 weeks of gestation and later in pregnancy may cause premature closure of the fetal ductus arteriosus.
Oligohydramnios/Neonatal Renal Impairment:Published studies and postmarketing reports describe maternal NSAID use at about 20 weeks gestation or later in pregnancy associated with fetal renal dysfunction leading to oligohydramnios, and in some cases, neonatal renal impairment. These adverse outcomes are seen, on average, after days to weeks of treatment, although oligohydramnios has been infrequently reported as soon as 48 hours after NSAID initiation. In many cases, but not all, the decrease in amniotic fluid was transient and reversible with cessation of the drug. There have been a limited number of case reports of maternal NSAID use and neonatal renal dysfunction without oligohydramnios, some of which were irreversible. Some cases of neonatal renal dysfunction required treatment with invasive procedures, such as exchange transfusion or dialysis.
Methodological limitations of these postmarketing studies and reports include lack of a control group; limited information regarding dose, duration, and timing of drug exposure; and concomitant use of other medications. These limitations preclude establishing a reliable estimate of the risk of adverse fetal and neonatal outcomes with maternal NSAID use. Because the published safety data on neonatal outcomes involved mostly preterm infants, the generalizability of certain reported risks to the full-term infant exposed to NSAIDs through maternal use is uncertain.

LABOR & DELIVERY

In rat studies with NSAIDs, as with other drugs known to inhibit prostaglandin synthesis, an increased incidence of dystocia, delayed parturition, and decreased pup survival occurred. The effects of tolmetin on labor and delivery in pregnant women are unknown.

NURSING MOTHERS

Tolmetin sodium has been shown to be secreted in human milk. Because of the potential for serious adverse reactions in nursing infants from tolmetin sodium, a decision should be made whether to discontinue nursing or to discontinue the drug, taking into account the importance of the drug to the mother.

PEDIATRIC USE

Safety and effectiveness in pediatric patients below the age of 2 years have not been established.

GERIATRIC USE

As with any NSAIDs, caution should be exercised in treating the elderly (65 years and older).

ADVERSE REACTIONS

The adverse reactions which have been observed in clinical trials encompass observations in about 4,370 patients treated with TOLECTIN, over 800 of whom have undergone at least one year of therapy. These adverse reactions, reported below by body system, are among those typical of nonsteroidal anti-inflammatory drugs and, as expected, gastrointestinal complaints were most frequent. In clinical trials with tolmetin, about 10% of patients dropped out because of adverse reactions, mostly gastrointestinal in nature.
Incidence Greater Than 1%:The following adverse reactions which occurred more frequently than 1 in 100 were reported in controlled clinical trials:
Gastrointestinal:nausea (11%), dyspepsia*, gastrointestinal distress*, abdominal pain*, diarrhea*, flatulence*, vomiting*, constipation, gastritis, and peptic ulcer. Forty percent of the ulcer patients had a prior history of peptic ulcer disease and/or were receiving concomitant anti-inflammatory drugs including corticosteroids, which are known to produce peptic ulceration.
Body as a Whole:headache*, asthenia*, chest pain
Cardiovascular:elevated blood pressure*, edema*
Central Nervous System:dizziness*, drowsiness, depression
Metabolic/Nutritional:weight gain*, weight loss*
Dermatologic:skin irritation
Special Senses:tinnitus, visual disturbance
Hematologic:Small and transient decreases in hemoglobin and hematocrit not associated with gastrointestinal bleeding have occurred. These are similar to changes reported with other nonsteroidal anti-inflammatory drugs.
Urogenital:elevated BUN, urinary tract infection
*Reactions occurring in 3% to 9% of patients treated with TOLECTIN. Reactions occurring in fewer than 3% of the patients are unmarked.
Incidence Less Than 1%:(Causal Relationship Probable) The following adverse reactions were reported less frequently than 1 in 100 in controlled clinical trials or were reported since marketing. The probability exists that there is a causal relationship between TOLECTIN and these adverse reactions.
Gastrointestinal:gastrointestinal bleeding with or without evidence of peptic ulcer, perforation, glossitis, stomatitis, hepatitis, liver function abnormalities
Body as a Whole:anaphylactoid reactions, fever, lymphadenopathy, serum sickness
Hematologic:hemolytic anemia, thrombocytopenia, granulocytopenia, agranulocytosis
Cardiovascular:congestive heart failure in patients with marginal cardiac function
Dermatologic:urticaria, purpura, erythema multiforme, toxic epidermal necrolysis
Urogenital:hematuria, proteinuria, dysuria, renal failure
Incidence Less Than 1%:(Causal Relationship Unknown) Other adverse reactions were reported less frequently than 1 in 100 in controlled clinical trials or were reported since marketing, but a causal relationship between tolmetin and the reaction could not be determined. These rarely reported reactions are being listed as alerting information for the physician since the possibility of a causal relationship cannot be excluded.
Body as a Whole:epistaxis
Special Senses:optic neuropathy, retinal and macular changes

To report SUSPECTED ADVERSE REACTIONS, contact Poly Pharmaceuticals, Inc. at 1-256-270-7552 or FDA at 1-800-FDA-1088 or www.fda.gov/medwatch.

MANAGEMENT OF OVERDOSAGE

In the event of overdosage, the stomach should be emptied by inducing vomiting or by gastric lavage followed by the administration of activated charcoal.

DOSAGE & ADMINISTRATION

Carefully consider the potential benefits and risks of TOLECTIN and other treatment options before deciding to use TOLECTIN. Use the lowest effective dose for the shortest duration consistent with individual patient treatment goals (see WARNINGS).
After observing the response to initial therapy with TOLECTIN, the dose and frequency should be adjusted to suit an individual patient’s needs.
For the relief of rheumatoid arthritis or osteoarthritis, the recommended starting dose for adults is 400 mg three times daily (1200 mg daily), preferably including a dose on arising and a dose at bedtime. To achieve optimal therapeutic effect the dose should be adjusted according to the patient’s response after 1 or 2 weeks. Control is usually achieved at doses of 600 mg to 1800 mg daily in divided doses (generally t.i.d.). Doses larger than 1800 mg/day have not been studied and are not recommended.
For the relief of juvenile rheumatoid arthritis, the recommended starting dose for pediatric patients (2 years and older) is 20 mg/kg/day in divided doses (t.i.d. or q.i.d.). When control has been achieved, the usual dose ranges from 15 to
30 mg/kg/day. Doses higher than 30 mg/kg/day have not been studied, and, therefore, are not recommended.
A therapeutic response to TOLECTIN can be expected in a few days to a week. Progressive improvement can be anticipated during succeeding weeks of therapy. If gastrointestinal symptoms occur, TOLECTIN can be
administered with antacids other than sodium bicarbonate. TOLECTIN bioavailability and pharmacokinetics are not significantly affected by acute or chronic administration of magnesium and aluminum hydroxides; however,
bioavailability is affected by food or milk (see PRECAUTIONS: Drug-Food Interaction).

HOW SUPPLIED

TOLECTIN Tablets, USP are available containing 738 mg of tolmetin sodium, USP as the dihydrate in an amount equivalent to 600 mg of tolmetin. The 600 mg tablets are a beige, film-coated, oval-shaped, biconvex, beveled-edge tablet debossed with “R 25” on one side of the tablet and plain on the other side. They are available as follows:

Bottles of 30 Tablets NDC 50991-988-30
Store at 20° to 25°C (68° to 77°F). [See USP Controlled Room Temperature.]
Protect from light.
Dispense in a tight, light-resistant container as defined in the USP using a child-resistant closure.
Manufactured for:
Poly Pharmaceuticals, Inc.
Owens Cross Roads, AL 35763

Issued: 02/2024
PHARMACIST:Dispense a Medication Guide with each prescription.

SPL MEDGUIDE

Medication Guide for Nonsteroidal Anti-inflammatory Drugs (NSAIDs)
What is the most important information I should know about medicines called Nonsteroidal Anti-inflammatory Drugs (NSAIDs)?
NSAIDs can cause serious side effects, including:
• Increased risk of a heart attack or stroke that can lead to death. This risk may happen early in treatment and may increase:
° with increasing doses of NSAIDs
° with longer use of NSAIDs
Do not take NSAIDs right before or after a heart surgery called a “coronary artery bypass graft (CABG).”
Avoid taking NSAIDs after a recent heart attack, unless your healthcare provider tells you to. You may have an increased risk of another heart attack if you take NSAIDs after a recent heart attack.
• Increased risk of bleeding, ulcers, and tears (perforation) of the esophagus (tube leading from the mouth to the stomach), stomach and intestines:
° anytime during use
° without warning symptoms
° that may cause death
The risk of getting an ulcer or bleeding increases with:
° past history of stomach ulcers, or stomach or intestinal bleeding with use of NSAIDs
° taking medicines called “corticosteroids”, “anticoagulants”, “SSRIs”, or “SNRIs”
° increasing doses of NSAIDs
° older age
° poor health
° advanced liver disease
° bleeding problems
° longer use of NSAID
° smoking
° drinking alcohol
NSAIDs should only be used:
° exactly as prescribed
° at the lowest dose possible for your treatment
° for the shortest time needed
What are NSAIDs?
NSAIDs are used to treat pain and redness, swelling, and heat (inflammation) from medical conditions such as different types of arthritis, menstrual cramps, and other types of short-term pain.
Who should not take NSAIDs?
Do not take NSAIDs:

- if you have had an asthma attack, hives, or other allergic reaction with aspirin or any other NSAIDs.
- right before or after heart bypass surgery.

Before taking NSAIDs, tell your healthcare provider about all of your medical conditions, including if you:

- have liver or kidney problems
- have high blood pressure
- have asthma
- are pregnant or plan to become pregnant. Taking NSAIDs at about 20 weeks of pregnancy or later may harm your unborn baby. If you need to take NSAIDs for more than 2 days when you are between 20 and 30 weeks of pregnancy, your healthcare provider may need to monitor the amount of fluid in your womb around your baby. You should not take NSAIDs after about 30 weeks of pregnancy.
- are breastfeeding or plan to breast feed.

Tell your healthcare provider about all of the medicines you take, including prescription or over-the-counter medicines, vitamins or herbal supplements.
NSAIDs and some other medicines can interact with each other and cause serious side effects. Do not start taking any new medicine without talking to your healthcare provider first.
What are the possible side effects of NSAIDs?
NSAIDs can cause serious side effects, including:
See “What is the most important information I should know about medicines called Nonsteroidal Anti-inflammatory Drugs (NSAIDs)?”

- new or worse high blood pressure
- heart failure
- liver problems including liver failure
- kidney problems including kidney failure
- low red blood cells (anemia)
- life-threatening skin reactions
- life threatening allergic reactions
- Other side effects of NSAIDs include:stomach pain, constipation, diarrhea, gas, heartburn, nausea, vomiting, and dizziness.

Get emergency help right away if you get any of the following symptoms:

- shortness of breath or trouble breathing
- chest pain
- weakness in one part or side of your body
- slurred speech
- swelling of the face or throat

Stop taking your NSAID and call your healthcare provider right away if you get any of the following symptoms:

- nausea
- more tired or weaker than usual
- diarrhea
- itching
- your skin or eyes look yellow
- indigestion or stomach pain
- flu-like symptoms
- vomit blood
- there is blood in your bowel movement or it is black and sticky like tar
- unusual weight gain
- skin rash or blisters with fever
- swelling of the arms, legs, hands and feet

If you take too much of your NSAID, call your healthcare provider or get medical help right away.
These are not all the possible side effects of NSAIDs. For more information, ask
your healthcare provider or pharmacist about NSAIDs.
Call your doctor for medical advice about side effects. You may report side effects to FDA at 1-800-FDA-1088.
Other information about NSAIDs

- Aspirin is an NSAID but it does not increase the chance of a heart attack. Aspirin can cause bleeding in the brain, stomach, and intestines. Aspirin can also cause ulcers in the stomach and intestines.
- Some NSAIDs are sold in lower doses without a prescription (over-the-counter). Talk to your healthcare provider before using over-the-counter NSAIDs for more than 10 days.

General information about the safe and effective use of NSAIDs
Medicines are sometimes prescribed for purposes other than those listed in a Medication Guide. Do not use NSAIDs for a condition for which they were not prescribed. Do not give NSAIDs to other people, even if they have the same symptoms that you have. They may harm them.
If you would like more information about NSAIDs, talk with your healthcare provider. You can ask your pharmacist or healthcare provider for information about NSAIDs that is written for health professionals.
This Medication Guide has been approved by the U.S. Food and Drug Administration.
The brands listed are trademarks of their respective owners.
Manufactured for:
Rising Pharma Holdings, Inc.
East Brunswick, NJ 08816
Issued: 04/2023
200607
MGR82501-00